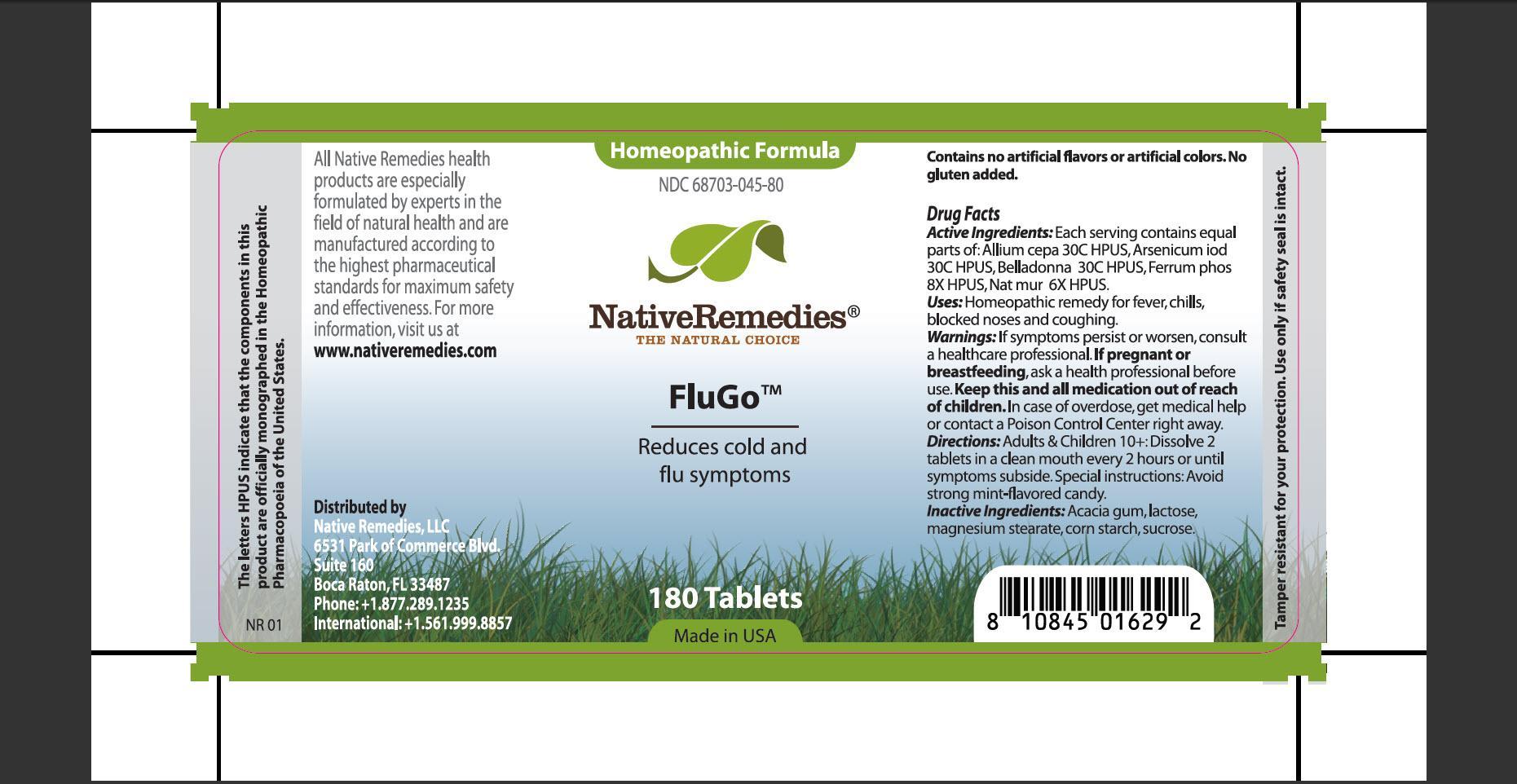 DRUG LABEL: FluGo
NDC: 68703-045 | Form: TABLET
Manufacturer: Native Remedies, LLC
Category: homeopathic | Type: HUMAN OTC DRUG LABEL
Date: 20120906

ACTIVE INGREDIENTS: ONION 30 [hp_C]/1 1; ARSENIC TRIIODIDE 30 [hp_C]/1 1; ATROPA BELLADONNA 30 [hp_C]/1 1; FERROSOFERRIC PHOSPHATE 8 [hp_X]/1 1; SODIUM CHLORIDE 6 [hp_X]/1 1
INACTIVE INGREDIENTS: ACACIA; LACTOSE; MAGNESIUM STEARATE; STARCH, CORN; SUCROSE

FluGo

PURPOSE

Reduces cold and flu symptoms

ACTIVE INGREDIENT

Active Ingredients: Each serving contains equal parts of: Allium cepa 30C HPUS, Arsenicum iod 30C HPUS, Belladonna 30C HPUS, Ferrum phos 8X HPUS, Nat mur 6X HPUS.

INDICATIONS AND USAGE

Uses: Homeopathic remedy for fever, chills, blocked noses and coughing.

WARNINGS

Warnings: If symptoms persist or worsen, consult a healthcare professional.

PREGNANCY OR BREAST FEEDING

If pregnant or breastfeeding, ask a health professional before use.

KEEP OUT OF REACH OF CHILDREN

Keep this and all medication out of reach of children.

OVERDOSAGE

In case of overdose, get medical help or contact a Poison Control Center right away.

DOSAGE AND ADMINISTRATION

Directions: Adults and Children 10+: Dissolve 2 tablets in a clean mouth every 2 hours or until symptoms subside. Special instructions: Avoid strong mint-flavored candy.

INACTIVE INGREDIENT

Inactive Ingredients: Acacia gum, lactose, magnesium stearate, corn starch, sucrose.

PATIENT COUNSELING INFORMATION

The letters HPUS indicate that the components in this product are officially monographed in the Homeopathic Pharmacopoeia of the United States.

All Native Remedies health products are especially formulated by experts in the field of natural health and are manufactured according to the highest pharmaceutical standards for maximum safety and effectiveness. For more information, visit us at www.nativeremedies.com

Distributed by
Native Remedies, LLC
6531 Park of Commerce Blvd.
Suite 160
Boca Raton, FL 33487
Phone: +1.877.289.1235
International: +1.561.999.8857

Contains no artificial flavors or artificial colors. No gluten added.

STORAGE AND HANDLING

Tamper resistant for your protection. Use only if safety seal is intact.